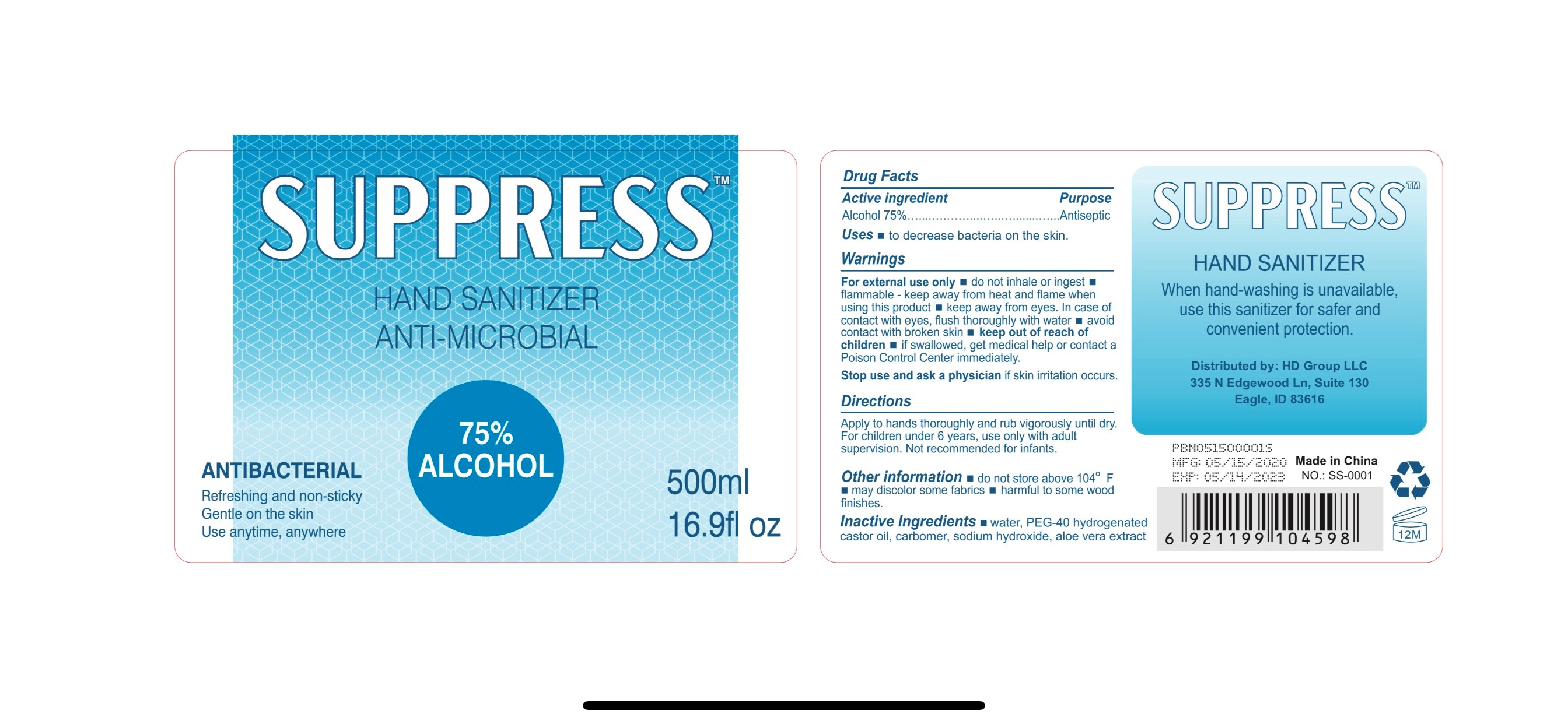 DRUG LABEL: SUPPRESS Hand Sanitizer
NDC: 77343-111 | Form: GEL
Manufacturer: HD Group LLC
Category: otc | Type: HUMAN OTC DRUG LABEL
Date: 20220114

ACTIVE INGREDIENTS: ALCOHOL 75 mL/100 mL
INACTIVE INGREDIENTS: SODIUM HYDROXIDE; ALOE VERA LEAF; PEG-40 CASTOR OIL; CARBOMER 940; WATER

SUPPRESS Hand Sanitizer

Active Ingredient(s)

Alcohol 75% v/v. Purpose: Antiseptic

Purpose

Antiseptic, Hand Sanitizer

Use

to decrease bacteria on the skin.

Warnings

For external use only. Do not inhale or ingest. Flammable. Keep away from heat or flame when using this product.

Do not use

- in children less than 2 months of age
- on open skin wounds

When using this product keep away from eyes. In case of contact with eyes, flush thoroughly with water. Avoid contact with broken skin.

Stop use and ask a physician if skin irritation occurs.

Keep out of reach of children. If swallowed, get medical help or contact a Poison Control Center immediately.

Directions

- Apply to hands thoroughly and rub vigorously until dry.
- For children under 6 years, use only with adult supervision.
- Not recommended for infants.

Other information

- Do not store above 104F (40C)
- May discolor some fabrics
- harmful to some wood finishes

Inactive ingredients

purified water USP

PEG-40 hydrogenated castor oil

carbomer

sodium hydroxide

aloe vera extract

Package Label - Principal Display Panel

500 mL NDC: 77343-111-01

Distributed By:

Distributed by: HD Group LLC 335 N Edgewood Ln, Suite 130 Eagle, ID 83616